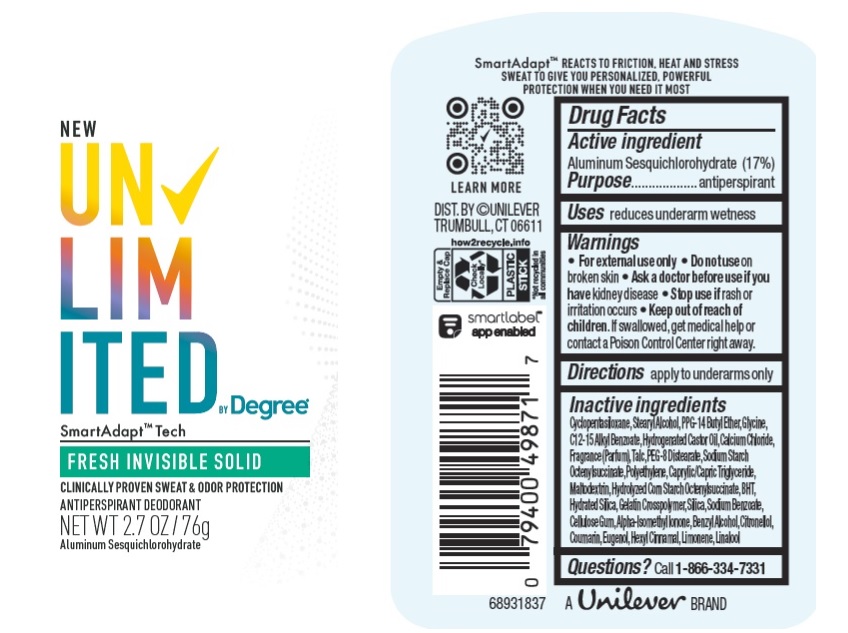 DRUG LABEL: Unlimited by Degree
NDC: 64942-2007 | Form: STICK
Manufacturer: Conopco Inc. d/b/a/ Unilever
Category: otc | Type: HUMAN OTC DRUG LABEL
Date: 20241106

ACTIVE INGREDIENTS: ALUMINUM SESQUICHLOROHYDRATE 17 g/100 g
INACTIVE INGREDIENTS: BENZYL ALCOHOL; .BETA.-CITRONELLOL, (R)-; COUMARIN; EUGENOL; LIMONENE, (+)-; HYDRATED SILICA; SODIUM BENZOATE; ISOMETHYL-.ALPHA.-IONONE; .ALPHA.-HEXYLCINNAMALDEHYDE; GLYCINE; ALKYL (C12-15) BENZOATE; HYDROGENATED CASTOR OIL; CALCIUM CHLORIDE; CYCLOMETHICONE 5; PPG-14 BUTYL ETHER; STEARYL ALCOHOL; BUTYLATED HYDROXYTOLUENE; SILICON DIOXIDE; MALTODEXTRIN; PEG-8 DISTEARATE; TALC; CARBOXYMETHYLCELLULOSE SODIUM, UNSPECIFIED FORM; LINALOOL, (+/-)-; HIGH DENSITY POLYETHYLENE; MEDIUM-CHAIN TRIGLYCERIDES

Unlimited by Degree Fresh Invisible Solid Antiperspirant Deodorant

Drug Facts

Active ingredient

Aluminum Sesquichlorohydrate (17%)

Purpose

antiperspirant

Uses

reduces underarm wetness

Warnings

• For external use only.
• Do not use on broken skin .
• Ask a doctor before use if you have kidney disease.
• Stop use if rash or irritation occurs.

• Keep out of reach of children.

If swallowed, get medical help or contact a Poison Control Center right away.

Directions

apply to underarms only

Inactive ingredients

Cyclopentasiloxane, Stearyl Alcohol, PPG-14 Butyl Ether, Glycine, C12-15 Alkyl Benzoate, Hydrogenated Castor Oil, Calcium Chloride, Fragrance (Parfum), Talc, PEG-8 Distearate, Sodium Starch Octenylsuccinate, Polyethylene, Caprylic/Capric Triglyceride,, Maltodextrin, Hydrolyzed Corn Starch Octenylsuccinate, BHT, Hydrated Silica, Gelatin Crosspolymer, Silica, Sodium Benzoate, Cellulose Gum, Alpha-Isomethyl Ionone, Benzyl Alcohol, Citronellol, Coumarin, Eugenol, Hexyl Cinnama,, Limonene, Linalool

Questions?

Call toll-free 1-866-334-7331